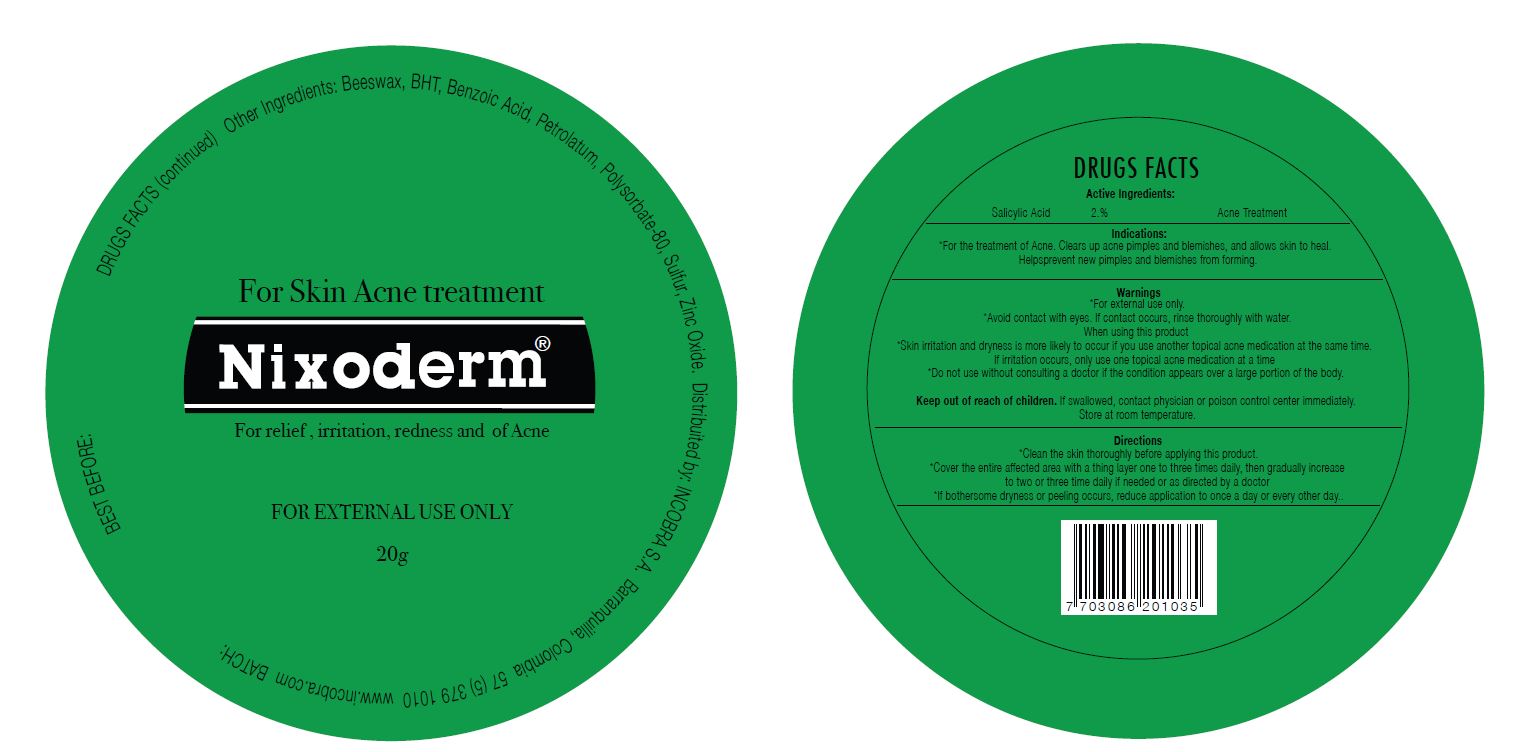 DRUG LABEL: Nixoderm Unguento
NDC: 70344-001 | Form: OINTMENT
Manufacturer: Laboratorios Incobra S.A.
Category: otc | Type: HUMAN OTC DRUG LABEL
Date: 20160210

ACTIVE INGREDIENTS: SALICYLIC ACID 2 g/100 g
INACTIVE INGREDIENTS: YELLOW WAX; BUTYLATED HYDROXYTOLUENE; BENZOIC ACID; PETROLATUM; POLYSORBATE 80; SULFUR; ZINC OXIDE

Active Ingredients:

Salicylic Acid 2%

PURPOSE

Acne Treatment

Keep out of reach of children. If swallowed, contact physician or poison control center immediately.

INDICATIONS AND USAGE

For Skin Acne treatment

For relief, irritation, redness and of Acne

Indications:

*For the treatment of Acne. Clears up acne pimples and blemishes, and allows skin to heal. Helpsprevent new pimples and blemishes from forming.

Directions:

*Clean the skin thoroughly before applying this product.

*Cover the entire affected area with a thing layer one to three times daily, then gradually increase to two or three time daily if needed or as directed by a doctor

*If bothersome dryness or peeling occurs, reduce application to once a day or every other day

Warnings:

*For external use only.

*Avoid contact with eyes. If contact occurs, rinse thoroughly with water

When using this product

*Skin irritation and dryness is more likely to occur if you use another topical acne medication at the same time. If irritation occurs, only use only topical acne medication at a time

*Do not use without consulting a doctor if the condition appears over a large portion of the body.

Store at room temperature.

INACTIVE INGREDIENT

Other Ingredients: beeswax, BHT, benzoic acid, petrolatum, polysorbate 80, sulfur, zinc oxide.